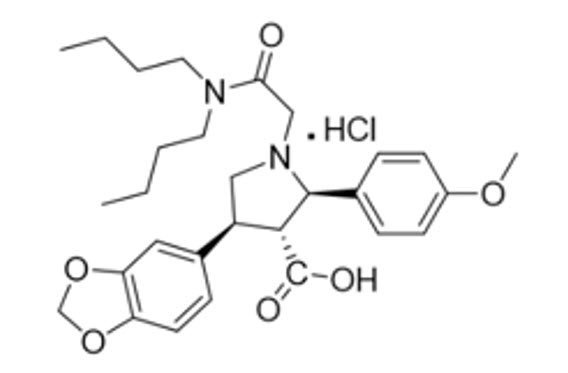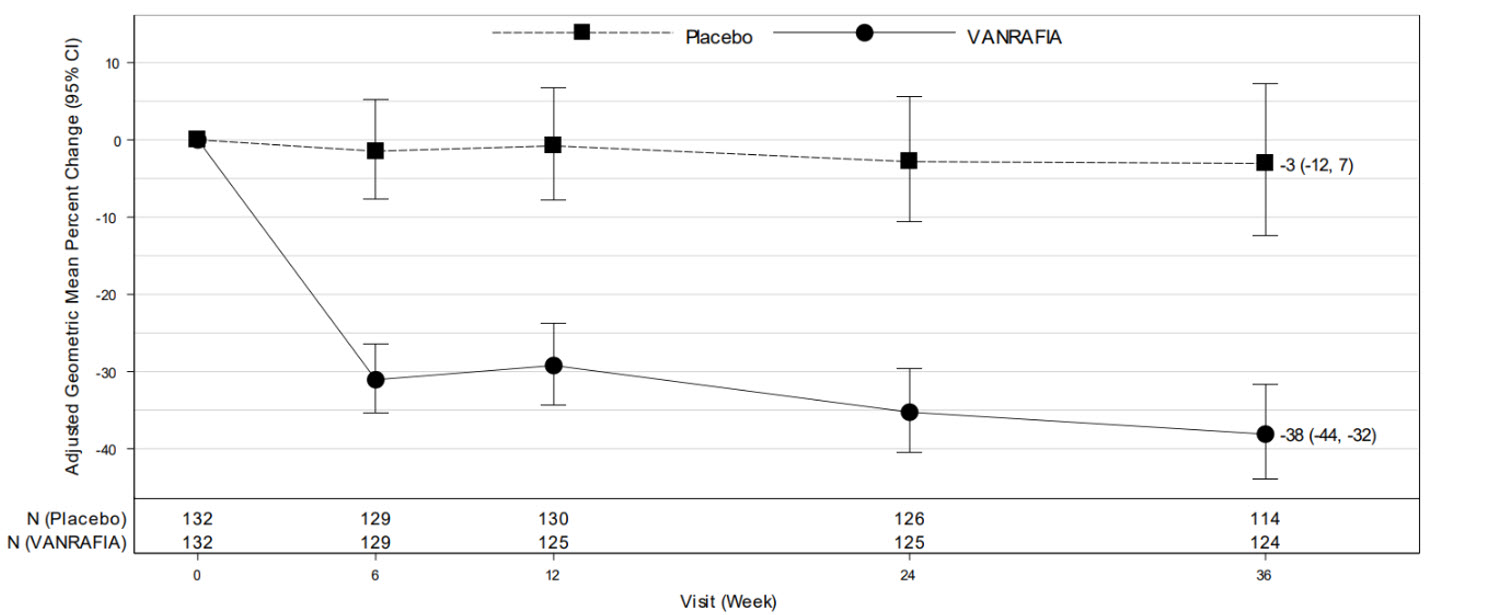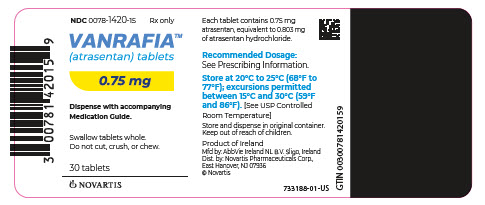 DRUG LABEL: VANRAFIA
NDC: 0078-1420 | Form: TABLET, FILM COATED
Manufacturer: Novartis Pharmaceuticals Corporation
Category: prescription | Type: HUMAN PRESCRIPTION DRUG LABEL
Date: 20250606

ACTIVE INGREDIENTS: ATRASENTAN HYDROCHLORIDE 0.75 mg/1 1
INACTIVE INGREDIENTS: CROSPOVIDONE, UNSPECIFIED; GLYCERYL DIBEHENATE; HYPROMELLOSE, UNSPECIFIED; LACTOSE MONOHYDRATE; CYSTEINE HYDROCHLORIDE; POLYETHYLENE GLYCOL, UNSPECIFIED; SILICON DIOXIDE

HIGHLIGHTS OF PRESCRIBING INFORMATION

These highlights do not include all the information needed to use VANRAFIA safely and effectively. See full prescribing information for VANRAFIA.
VANRAFIA™ (atrasentan) tablets, for oral use
Initial U.S. Approval: 2025

WARNING: EMBRYO-FETAL TOXICITY

See full prescribing information for complete boxed warning.

- VANRAFIA may cause major birth defects if used during pregnancy (4.1, 5.1, 8.1)
- Exclude pregnancy before start of treatment. (2.1, 4.1, 5.1, 8.3)
- Use effective contraception before start of treatment, during treatment and two weeks after treatment. (4.1, 5.1, 8.3)
- Discontinue VANRAFIA if pregnancy occurs. (4.1, 5.1)

1 INDICATIONS AND USAGE

VANRAFIA is an endothelin receptor antagonist indicated to reduce proteinuria in adults with primary immunoglobulin A nephropathy (IgAN) at risk of rapid disease progression, generally a urine protein-to-creatinine ratio (UPCR) ≥ 1.5 g/g. (1)

This indication is approved under accelerated approval based on a reduction of proteinuria. It has not been established whether VANRAFIA slows kidney function decline in patients with IgAN. Continued approval for this indication may be contingent upon verification and description of clinical benefit in a confirmatory clinical trial. (1)

2 DOSAGE AND ADMINISTRATION

- 0.75 mg orally once daily with or without food (2.2)

3 DOSAGE FORMS AND STRENGTHS

- Tablets: 0.75 mg (3)

4 CONTRAINDICATIONS

- Pregnancy (4.1)
- Hypersensitivity (4.2)

5 WARNINGS AND PRECAUTIONS

- Hepatotoxicity (5.2)
- Fluid Retention (5.3)
- Decreased Sperm Counts (5.4, 8.3)

6 ADVERSE REACTIONS

Most common adverse reactions (incidence ≥ 5%) were peripheral edema and anemia. (6.1)

To report SUSPECTED ADVERSE REACTIONS, contact Novartis Pharmaceuticals Corporation at 1-888-669-6682 or FDA at 1-800-FDA-1088 or www.fda.gov/medwatch.

7 DRUG INTERACTIONS

- Strong or moderate CYP3A inducers: Avoid concomitant use. (7.1)
- OATP1B1/1B3 inhibitors: Avoid concomitant use. (7.1)

8 USE IN SPECIFIC POPULATIONS

- Lactation: Advise not to breastfeed. (8.2)

FULL PRESCRIBING INFORMATION

WARNING: EMBRYO-FETAL TOXICITY

VANRAFIA is contraindicated for use in pregnant patients; it may cause major birth defects based on animal data [see Contraindications (4.1), Warnings and Precautions (5.1), Use in Specific Populations (8.1)]. Exclude pregnancy prior to initiation of treatment with VANRAFIA. Advise use of effective contraception before the initiation of treatment, during treatment, and for two weeks after discontinuation of treatment with VANRAFIA. Stop VANRAFIA as soon as possible if the patient becomes pregnant [see Dosage and Administration (2.1), Contraindications (4.1), Warnings and Precautions (5.1), Use in Specific Populations (8.1, 8.3)].

1 INDICATIONS AND USAGE

VANRAFIA is indicated to reduce proteinuria in adults with primary immunoglobulin A nephropathy (IgAN) at risk of rapid disease progression, generally a urine protein-to-creatinine ratio (UPCR) ≥ 1.5 g/g.

This indication is approved under accelerated approval based on a reduction of proteinuria [see Clinical Studies (14.1)]. It has not been established whether VANRAFIA slows kidney function decline in patients with IgAN. Continued approval for this indication may be contingent upon verification and description of clinical benefit in a confirmatory clinical trial.

2 DOSAGE AND ADMINISTRATION

2.1 Pregnancy Testing

Exclude pregnancy before initiating VANRAFIA [see Warnings and Precautions (5.1), Use in Specific Populations (8.1, 8.3)].

2.2 Recommended Dosage

The recommended dose of VANRAFIA is 0.75 mg administered orally once daily with or without food [see Clinical Pharmacology (12.3)].

Swallow tablets whole. Do not cut, crush, or chew.

If a dose or doses are missed, take the prescribed dose at the next scheduled time. Do not double the dose to make up for a missed dose.

3 DOSAGE FORMS AND STRENGTHS

VANRAFIA 0.75 mg: film-coated, round, biconvex, white to off-white tablet debossed with “7” on one side and unmarked on the other side.

4 CONTRAINDICATIONS

4.1 Pregnancy

Use of VANRAFIA is contraindicated in patients who are pregnant [see Dosage and Administration (2.1), Warnings and Precautions (5.1), Use in Specific Populations (8.1)].

4.2 Hypersensitivity

VANRAFIA is contraindicated in patients with a history of a hypersensitivity reaction to atrasentan or any component of the product.

5 WARNINGS AND PRECAUTIONS

5.1 Embryo-Fetal Toxicity

Based on data from animal reproduction studies, VANRAFIA may cause fetal harm when administered to a pregnant patient and is contraindicated during pregnancy. The available human data for endothelin receptor antagonists do not establish the presence or absence of major birth defects related to the use of VANRAFIA. Counsel patients who can become pregnant of the potential risk to a fetus. Exclude pregnancy prior to initiation of treatment with VANRAFIA. Advise patients to use effective contraception prior to initiation of treatment, during treatment, and for two weeks after discontinuation of treatment with VANRAFIA [see Dosage and Administration (2.1) and Use in Specific Populations (8.1, 8.3)]. When pregnancy is detected, discontinue VANRAFIA as soon as possible [see Dosage and Administration (2.1), Contraindications (4.1), Use in Specific Populations (8.1, 8.3)].

5.2 Hepatotoxicity

Some endothelin receptor antagonists (ERAs) have caused elevations of aminotransferases, hepatotoxicity, and liver failure. Asymptomatic and transient transaminase elevations have been observed with VANRAFIA [see Adverse Reactions (6.1)]. Obtain liver enzyme testing before initiating VANRAFIA and repeat during treatment as clinically indicated. In patients with elevated aminotransferases at baseline (>3 × upper limit of normal [ULN]), consider periodic liver test monitoring. Do not initiate VANRAFIA in patients with severe hepatic impairment.

Advise patients to report symptoms suggesting hepatic injury (nausea, vomiting, right upper quadrant pain, fatigue, anorexia, jaundice, dark urine, fever, or itching). If clinically relevant aminotransferase elevations occur, or if elevations are accompanied by an increase in bilirubin >2 x ULN, or by clinical symptoms of hepatotoxicity, discontinue VANRAFIA. Consider re-initiation of VANRAFIA when hepatic enzyme levels normalize in patients who have not experienced clinical symptoms of hepatotoxicity or jaundice.

5.3 Fluid Retention

Fluid retention may occur with ERAs and has been observed in clinical studies with VANRAFIA [see Adverse Reactions (6.1)]. VANRAFIA has not been evaluated in IgAN patients with heart failure. If clinically significant fluid retention develops, consider initiating or increasing diuretic treatment and interrupting VANRAFIA treatment.

5.4 Decreased Sperm Counts

VANRAFIA, similar to other ERAs, may have an adverse effect on spermatogenesis. Counsel men about potential effects on fertility [see Use in Specific Populations (8.3) and Nonclinical Toxicology (13.1)].

6 ADVERSE REACTIONS

The following clinically significant adverse reactions are described elsewhere in the labeling:

- Embryo-fetal Toxicity [see Warnings and Precautions (5.1)]
- Hepatotoxicity [see Warnings and Precautions (5.2)]
- Fluid Retention [see Warnings and Precautions (5.3)]
- Decreased Sperm Counts [see Warnings and Precautions (5.4)]

6.1 Clinical Trials Experience

Because clinical trials are conducted under widely varying conditions, adverse reaction rates observed in the clinical trials of a drug cannot be directly compared to rates in the clinical trials of another drug and may not reflect the rates observed in practice.

The safety of VANRAFIA was evaluated in ALIGN (NCT04573478), a randomized, double-blind, placebo controlled clinical study in 403 adults with IgAN [see Clinical Studies (14.1)]. The median duration of treatment was 47 weeks (range: 0 to 128 weeks). The most common adverse reactions (≥ 5%) with VANRAFIA were peripheral edema and anemia. Table 1 describes the adverse reactions that occurred in ≥ 2% of patients treated with VANRAFIA and higher than placebo in the ALIGN study.

Table 1: Adverse Reactions Reported in ≥ 2% of Adult Patients with IgAN Treated with VANRAFIA and Higher than Placebo in ALIGN
Adverse Reaction | VANRAFIA (N = 201) n (%) | Placebo (N = 202) n (%)
Peripheral edema* | 21 (10%) | 14 (7%)
Anemia* | 12 (6%) | 2 (1%)
Liver transaminase elevation** | 4 (2%) | 2 (1%)
*Includes related terms
**Elevations in ALT or AST > 3-fold upper limit of normal (ULN)

Laboratory Tests and Vital Signs

Hemoglobin Decrease

At Week 36, the mean change in hemoglobin from baseline for those patients receiving VANRAFIA in the ALIGN study was -0.7 g/dL compared to -0.2 g/dL for those receiving placebo. The incidence of a hemoglobin decrease > 2 g/dL compared to baseline and below the lower limit of normal was greater for the VANRAFIA arm (12%) compared to the placebo arm (4%). These decreases are thought to be in part due to hemodilution. There were no treatment discontinuations due to anemia or hemoglobin decrease in the ALIGN study.

Blood Pressure Decrease

At Week 36, the mean change from baseline in systolic and diastolic blood pressure (BP) for patients receiving VANRAFIA in the ALIGN study was -4 mmHg and -4 mmHg, respectively, compared to +3 mmHg and +2 mmHg, respectively, in patients receiving placebo. Hypotension observed in VANRAFIA treated patients was mild or moderate in severity, rarely symptomatic, and did not necessitate treatment discontinuation.

7 DRUG INTERACTIONS

7.1 Effect of Other Drugs on VANRAFIA

Strong or Moderate CYP3A Inducers

Avoid concomitant use with a strong or moderate CYP3A inducer.

Atrasentan is a CYP3A substrate [see Clinical Pharmacology (12.3)]. Concomitant use with a strong and moderate CYP3A inducer is expected to decrease atrasentan exposure [see Clinical Pharmacology (12.3)], which may reduce VANRAFIA efficacy.

OATP1B1/1B3 Inhibitors

Avoid concomitant use with organic anion transporting polypeptides 1B1/1B3 (OATP1B1/1B3) inhibitors.

Atrasentan is a OATP1B1/1B3 substrate [see Clinical Pharmacology (12.3)]. Concomitant use with a OATP1B1/1B3 inhibitor increases atrasentan exposure [see Clinical Pharmacology (12.3)], which may increase the risk of VANRAFIA adverse reactions.

8 USE IN SPECIFIC POPULATIONS

8.1 Pregnancy

Risk Summary

Based on data from animal reproductive toxicity studies, VANRAFIA may cause fetal harm, including birth defects and fetal death, when administered to a pregnant patient and is contraindicated during pregnancy [see Contraindications (4.1)]. There are no available data on VANRAFIA use in pregnancy to evaluate for a drug-associated risk of major birth defects, miscarriage, or other adverse maternal or fetal outcomes. Available data from published literature and post-marketing surveillance over decades of use with products in the same pharmacologic class (ERA) have not identified an increased risk of major birth defects. However, these data are limited and do not establish the presence or absence of a drug-associated risk of major birth defects. Methodological limitations of these post marketing reports and published literature include lack of a control group; limited information regarding dose, duration, and timing of exposure; and missing data. These limitations preclude establishing a reliable estimate of the risk of adverse fetal and neonatal outcomes with maternal endothelin receptor antagonist use.

In animal reproduction studies, oral administration of atrasentan to pregnant rats and rabbits throughout organogenesis at doses that were below the maximum recommended human dose (MRHD) based on area under the curve (AUC) caused teratogenic effects in rats and rabbits (see Data). Advise pregnant patients of the potential risk to the fetus [see Contraindications (4.1)].

The background risk of major birth defects and miscarriage for the indicated population is unknown. All pregnancies have a background risk of birth defects, loss, or other adverse outcomes. In the U.S. general population, the estimated background risk of major birth defects and miscarriage in clinically recognized pregnancies is 2 to 4% and 15 to 20%, respectively.

Data

Animal Data

In embryo-fetal development studies in pregnant rats and rabbits, teratogenicity and/or embryo-fetal toxicity were observed.

In pregnant rats, oral administration of atrasentan throughout organogenesis at doses of 0.1, 0.3, 1.0, and 3.0 mg/kg/day resulted in developmental abnormalities primarily including the ear, lower jaw, or skull in all treated groups with detectable plasma exposures to atrasentan. The no adverse effect level of atrasentan plasma exposure was not determined. In pregnant rabbits, oral administration of atrasentan throughout organogenesis at doses of 0.1, 0.3, 1.0 and 3.0 mg/kg/day resulted in visceral malformations including deformities in the cardiovascular system in all atrasentan-treated groups. The lowest detectable plasma exposures to atrasentan were approximately 0.2 times the AUC at the MRHD.

In the pre- and postnatal development study in rats, atrasentan was orally administered to pregnant rats at doses of 1, 10, or 100 mg/kg/day during the period from gestation Day 15 through lactation Day 20. No adverse effects on pre- and postnatal development were observed at doses up to 10 mg/kg/day which resulted in maternal exposure approximately 55 times the AUC at the MRHD. Higher exposure to atrasentan (dose of 100 mg/kg/day) increased pup mortality during the pre-weaning period, and increased heart weight which correlated histologically with myocardial hypertrophy.

8.2 Lactation

Risk Summary

There are no data on the presence of atrasentan in human milk, the effects on the breastfed infant, or the effect on milk production. Because of the potential for adverse reactions, such as fluid retention in breastfed infants, advise patients not to breastfeed during treatment with VANRAFIA.

8.3 Females and Males of Reproductive Potential

Based on data from animal reproductive toxicity studies, VANRAFIA may cause fetal harm, including birth defects and fetal death, when administered to a pregnant patient and is contraindicated during pregnancy [see Contraindications (4.1), Use in Specific Populations (8.1)].

Pregnancy Testing

Exclude pregnancy before initiating VANRAFIA in females of reproductive potential. The patient should contact their physician immediately for pregnancy testing if onset of menses is delayed or pregnancy is suspected. If pregnancy is confirmed, the physician should discuss with the patient the risks to the pregnancy and the fetus.

Contraception

Patients who can become pregnant while using VANRAFIA should use effective contraception prior to initiation of treatment, during treatment, and for two weeks after discontinuation of treatment with VANRAFIA to prevent pregnancy [see Warnings and Precautions (5.1)].

Infertility

Decreased sperm counts have been observed in some patients with diabetic kidney disease (DKD) receiving VANRAFIA 0.75 mg once daily with return to normal levels within approximately 3 months after drug discontinuation. This effect has not been studied in patients with IgAN [see Nonclinical Toxicology (13.1)].

8.4 Pediatric Use

The safety and efficacy of VANRAFIA in pediatric patients have not been established.

8.5 Geriatric Use

There were 29 (7%) patients 65 years of age and older in the ALIGN study of VANRAFIA. Of the total number of VANRAFIA-treated patients, 15 (7%) were 65 years to 75 years of age, and 3 (2%) were 75 years of age and older. No overall differences in safety and effectiveness were observed between these patients and younger patients.

8.6 Hepatic Impairment

No dose adjustment is required for patients with mild or moderate hepatic impairment. Do not initiate VANRAFIA in patients with severe hepatic impairment [see Warnings and Precautions (5.2)].

10 OVERDOSAGE

There is no experience with overdose of VANRAFIA. Atrasentan has been given in a single dose up to 139.5 mg and multiple doses up to 40 mg/day in healthy volunteers. Overdose of VANRAFIA may result in headache or vasodilation. In the event of an overdose, standard supportive measures should be taken, as required. Dialysis is unlikely to be effective because atrasentan is highly protein-bound.

11 DESCRIPTION

VANRAFIA contains atrasentan, an endothelin type A (ETA) receptor antagonist. The chemical name of atrasentan hydrochloride is (2R, 3R, 4S)-4-(1,3-benzodioxol-5-yl)-1-[2-(dibutylamino)-2-oxoethyl]-2-(4-methoxyphenyl)-3-pyrrolidinecarboxylic acid hydrochloride. Atrasentan hydrochloride has a molecular weight of 547.09 g/mol, a molecular formula of C29H38N2O6HCl and the following structural formula.

Atrasentan is a slightly hygroscopic white to off-white powder that is slightly soluble in water.

VANRAFIA is available as a film-coated tablet for oral administration. Each VANRAFIA tablet contains 0.75 mg atrasentan (equivalent to 0.803 mg of atrasentan hydrochloride) and contains the following excipients: crospovidone, glyceryl dibehenate, hypromellose, lactose monohydrate, L-cysteine hydrochloride monohydrate, polyethylene glycol, and silicon dioxide.

12 CLINICAL PHARMACOLOGY

12.1 Mechanism of Action

Atrasentan is an ETA receptor antagonist (Ki = 0.034 nM) with >1800-fold selectivity for the ETA receptor compared to the endothelin type B receptor (Ki = 63.3 nM). Endothelin (ET)-1 is thought to contribute to the pathogenesis of IgAN via the ETAR.

12.2 Pharmacodynamics

Dose-response information is not available. At the recommended dose regimen, no statistically significant exposure-response (E-R) relationship was identified between atrasentan exposure and the percentage reduction from baseline in UPCR at Week 36 over the observed atrasentan exposure range. Increased atrasentan exposure was associated with an increased incidence of anemia, but no association was observed between atrasentan exposure and hypotension or peripheral edema.

Cardiac Electrophysiology

At exposures 40% higher than the clinical exposure at the maximum recommended dose, clinically significant QTc interval prolongation was not observed.

12.3 Pharmacokinetics

Atrasentan area under the time concentration curve (AUC) is dose proportional across the 0.35 mg to 30 mg (0.47 to 40 times the approved recommended dosage) dose range. Atrasentan steady state plasma concentrations are reached within 7 days with 2- to 3-fold accumulation.

Absorption

Atrasentan time to peak plasma concentration (Tmax) is approximately 0.5 hour.

Effect of Food

No clinically significant differences in atrasentan pharmacokinetics were observed following administration with a high-fat meal (800 to 1000 Kcal, > 50% fat) in healthy subjects.

Distribution

Atrasentan steady-state apparent (oral) volume of distribution (Vd/F) is 1180 L. Atrasentan is > 99% bound to human plasma proteins, in vitro.

Elimination

Atrasentan effective half-life is approximately 24 to 41 hours with an apparent (oral) clearance (CL/F) of 19 L/h.

Metabolism

Atrasentan is extensively metabolized by CYP3A and multiple uridine 5'-diphospho-glucuronosyltransferases (UGTs) with approximately half via CYP3A and the remaining half via glucuronidation by multiple UGTs.

Excretion

After a single dose of radiolabeled atrasentan 10 mg to healthy subjects, approximately 86% of the dose was recovered in feces (5.5% as parent atrasentan). Renal excretion was minimal, with < 4% recovered in urine (negligible amounts of parent atrasentan).

Specific Populations

No clinically significant differences in the pharmacokinetics of atrasentan were observed based on age (19 to 77 years), sex, race, mild to severe renal impairment (eGFR 15 to 90 mL/min/1.73 m^2, estimated by CKD-EPI), or mild to moderate hepatic impairment (Child-Pugh class A or B). The effect of severe hepatic impairment (Child-Pugh class C) or end-stage renal disease (eGFR < 15 mL/min/1.73 m^2) on atrasentan pharmacokinetics is unknown.

Drug Interaction Studies

Clinical Studies and Model-Informed Approaches

Strong and moderate CYP3A inducers: Atrasentan Ctrough decreased by 90% following coadministration of a single dose of 10 mg VANRAFIA with rifampin (strong CYP3A inducer).

OATP1B1/1B3 inhibitors: Atrasentan Cmax was 4.3 times as high and AUC was 3.8 times as high following coadministration of a single dose of 0.75 mg VANRAFIA with cyclosporine (OATP1B1/1B3 inhibitor).

Strong CYP3A inhibitors: Atrasentan AUC increased by 90% following coadministration of a single dose of 10 mg VANRAFIA with ketoconazole (strong CYP3A inhibitor).

Other Drugs: No clinically significant differences in the pharmacokinetics of midazolam (CYP3A4 substrate), losartan (CYP2C9 and CYP3A4 substrate) or fexofenadine (P-gp substrate) were observed or expected when used concomitantly with VANRAFIA.

In Vitro Studies

CYP450 Enzymes: Atrasentan is a CYP3A substrate. Atrasentan inhibits in vitro CYP3A, CYP2B6, CYP2C8 and CYP2C9 and induces CYP3A and CYP2B6, but is not expected to cause clinically significant interactions with these CYP450 enzymes in the liver. Atrasentan does not inhibit CYP1A2, CYP2C19, or CYP2D6 and is not an inducer of CYP1A2.

Transporter Systems: Atrasentan is a substrate of P-gp and OATP1B1/1B3 but not a substrate of BCRP, MRP2/4, NTCP, OCT1, or OATP2B1. Atrasentan inhibits P-gp, OATP1B1, and OATP1B3, but not expected to cause clinically significant interactions. Atrasentan does not inhibit MRP, NTCP, OCT, OAT1, MATE1, or MATE2K.

13 NONCLINICAL TOXICOLOGY

13.1 Carcinogenesis, Mutagenesis, Impairment of Fertility

Carcinogenesis

In female rats orally administered atrasentan for 2 years, no atrasentan-related tumor findings were observed at exposures approximately 12 times the AUC at the MRHD. At a higher exposure (approximately 24 times the AUC at the MRHD, or 2 mg/kg/day), an increased incidence of benign uterine stromal polyps considered of low human relevance was observed. In male rats, no carcinogenic effects were observed at exposures approximately 100 times the AUC at the MRHD.

There were no atrasentan-related tumor findings observed in male and female transgenic mice administered atrasentan for 6 months at doses up to 60 mg/kg/day.

Mutagenesis

There was no evidence of mutagenicity or clastogenicity for atrasentan in in vitro bacteria reverse mutation and chromosomal aberration assays, or in an in vivo mouse micronucleus study.

Impairment of Fertility

In a fertility study, male rats were treated with atrasentan at doses of 5, 20, and 60 mg/kg/day and mated with untreated female rats. No adverse effects on male fertility were observed at 5 mg/kg/day, approximately 53 times the AUC at the MRHD. At higher doses, decreased numbers of implantation sites, reduced viable fetuses, and increased pre-implantation loss were observed in the untreated female rats mated with the treated male rats. These effects were reversible at 20 mg/kg/day, approximately 422 times the AUC at MRHD. In rats and dogs, testicular degeneration, dilatation of seminiferous tubules, interstitial edema of the testes, and prostate inflammation were observed at all doses tested, and a no adverse effect dose level could not be determined.

In a female rat fertility study, no reproductive toxicity was observed following oral administration during premating, mating, and early gestation at doses up to 100 mg/kg/day.

In female rats, cystic endometrial hyperplasia was observed at the lowest dose tested of 0.8 mg/kg/day.

14 CLINICAL STUDIES

14.1 IgA Nephropathy

The effect of VANRAFIA on proteinuria was assessed in a randomized, double-blind, placebo-controlled, multicenter, global study (ALIGN, NCT04573478) in adults with biopsy-proven primary IgAN, an eGFR ≥ 30 mL/min/1.73 m^2, and urine protein ≥ 1 g/day on a stable dose of maximally tolerated renin angiotensin system inhibitor. The study included two cohorts: a main cohort of 340 patients and an exploratory cohort of 64 patients who were also on a stable dose of sodium glucose co-transporter 2 inhibitor (SGLT2i) at baseline. Patients with chronic kidney disease due to another condition in addition to IgAN or those who had been recently treated with systemic immunosuppressants were excluded. Patients were randomized (1:1) to receive either VANRAFIA 0.75 mg or placebo once daily. RAS inhibitor therapy was continued throughout the study. Rescue immunosuppressive treatment could be initiated per investigator discretion during the trial.

The efficacy analysis included the first 270 patients in the main cohort who reached the Week 36 visit. At baseline, the mean age was 45 years (range: 19 to 77 years); 59% were male, 36% White, 57% Asian, 2% Black or African American and 5% other or not specified. At baseline, 60% had a history of hypertension, 1.5% had a history of type 2 diabetes, and 45% had hematuria based on urine dipstick. The mean baseline eGFR was 59 mL/min/1.73 m^2. The geometric mean baseline UPCR was 1.5 g/g sampled from a 24-hour urine and 15% of patients had proteinuria > 3.5 g/day.

The primary endpoint was the percent reduction in UPCR at Week 36 relative to baseline (see Table 2).

Table 2: Percent Reduction in UPCR at Week 36 Relative to Baseline in ALIGN
 | VANRAFIA on top of supportive carea (N = 135) | Placebo on top of supportive carea (N = 135)
% Reduction in UPCR (95% CI) at Week 36 relative to baselineb,d | 38% (32%, 44%) | 3% (-7%, 12%)
VANRAFIA versus placebo: % reduction in UPCR (95% CI) at Week 36 relative to baseline compared on a relative scalec,d | 36% (26%, 45%)
p-valuee | < 0.0001
aSupportive care: primarily a stable dose of maximally-tolerated RAS inhibitor therapy.
bLeast squares geometric mean ratio in UPCR (sampled from a 24-hr urine collection) to baseline was reported as a percent reduction along with the respective 95% confidence interval.
cThe estimate of the ratio of least squares geometric mean ratio in UPCR (sampled from a 24-hr urine collection) to baseline comparing VANRAFIA with placebo was reported as a relative percent reduction along with the respective 95% confidence interval and 2-sided p-value.
dMixed model repeated measures analysis included all observed UPCR data except for subjects with intercurrent events (i.e., restricted medication use, chronic dialysis, kidney transplant). These subjects had UPCR data excluded beginning at the start date of the earliest event. The only intercurrent events observed were restricted medication use, which occurred in 3.0% and 5.2% of VANRAFIA and placebo treated subjects, respectively.
eTwo-sided p-value statistically significant at the 0.01 level.
Abbreviations: CI, confidence interval; N, number of randomized subjects in each group in the main cohort; UPCR, urine protein-to-creatinine ratio; RAS, renin-angiotensin system.

The adjusted geometric mean percent change from baseline in UPCR over time is displayed in Figure 1.

Figure 1: Geometric Mean Percent Change from Baseline in UPCR by Visit in ALIGN

Adjusted % change relative to baseline in UPCR (sampled from a 24-hr urine collection) was estimated based on the MMRM analysis in Table 2.
N represents the number of evaluable subjects included in the analysis (i.e., with non-missing UPCR values and baseline covariates, and did not initiate restricted medication use, chronic dialysis, or kidney transplant) for each visit and treatment group.
Values reported in the figure were expressed as percent change from baseline and 95% CI, estimated from the regression model in Table 2.
Abbreviations: CI, confidence interval; MMRM, mixed model repeated measures; UPCR, urine protein-to-creatinine ratio.

The treatment effect on UPCR at Week 36 was consistent across subgroups including age, sex, race, baseline disease characteristics (such as baseline eGFR and proteinuria levels) within the main cohort. The treatment effect on UPCR at Week 36 was also consistent in the exploratory SGLT2i cohort.

16 HOW SUPPLIED/STORAGE AND HANDLING

VANRAFIA is supplied as follows:

- 0.75 mg tablets are film-coated, round, biconvex, white to off-white tablets debossed with “7” on one side and unmarked on the other side, packaged in a high-density polyethylene (HDPE) bottle containing a desiccant, with induction seal and child-resistant cap. Each bottle contains 30 tablets (NDC 0078-1420-15).

Storage

Store at 20°C to 25°C (68°F to 77°F). Excursions are permitted between 15°C and 30°C (59°F and 86°F). [See USP Controlled Room Temperature]. Store and dispense VANRAFIA in its original container.

17 PATIENT COUNSELING INFORMATION

Advise the patient to read the FDA-approved patient labeling (Medication Guide)

Embryo-Fetal Toxicity

Educate and counsel female patients of reproductive potential to use effective contraception prior to starting treatment with VANRAFIA, during treatment and for two weeks after treatment discontinuation. Patients who can become pregnant should have a negative pregnancy test prior to treatment with VANRAFIA [see Dosage and Administration (2.1), Contraindications (4.1), Warnings and Precautions (5.1), Use in Specific Populations (8.1, 8.3)].

Patients should be instructed to immediately contact their physician if they suspect they may be pregnant. Patients should seek additional contraceptive advice as needed.

Educate and counsel patients who can become pregnant on the use of emergency contraception in the event of unprotected sex or contraceptive failure.

Advise patients to contact their healthcare provider if they want to change the form of birth control which is used to ensure that another acceptable form of birth control is selected.

Hepatotoxicity

Some members of this pharmacological class are hepatotoxic. Educate patients on signs of hepatotoxicity. Advise patients that they should contact their doctor if they have unexplained nausea, vomiting, right upper quadrant pain, fatigue, anorexia, jaundice, dark urine, fever, or itching [see Warnings and Precautions (5.2)].

Fluid Retention

Educate patients on signs of fluid retention. Advise patients that they should contact their doctor if they have unusual weight increase or swelling of the ankles or legs [see Warnings and Precautions (5.3)].

Lactation

Advise patients not to breastfeed during treatment with VANRAFIA [see Use in Specific Populations (8.2)].

Other Risks Associated with VANRAFIA

Instruct patients that the risks associated with VANRAFIA also include the following:

- Decreases in sperm count [see Warnings and Precautions (5.4)]

Distributed by:
Novartis Pharmaceuticals Corporation
East Hanover, New Jersey 07936

© 2025 Novartis

T2025-18

MEDICATION GUIDE
VANRAFIA™ (van-rah-fee-ah)
(atrasentan)
tablets

What is the most important information I should know about VANRAFIA?
VANRAFIA can cause serious birth defects if taken during pregnancy.

- Females should not be pregnant when they start taking VANRAFIA or become pregnant during treatment with VANRAFIA or for two weeks after stopping treatment with VANRAFIA.
- Females who can become pregnant should have a negative pregnancy test before starting VANRAFIA.
  - Females who can become pregnant are those who:
    - have entered puberty, even if they have not started their menstrual period, and
    - have a uterus, and
    - have not gone through menopause. Menopause means that you have not had a menstrual period for at least 12 months for natural reasons, or that you have had your ovaries removed.
  - Females who cannot become pregnant are those who:
    - have not yet entered puberty, or
    - do not have a uterus, or
    - have gone through menopause. Menopause means that you have not had a menstrual period for at least 12 months for natural reasons, or that you have had your ovaries removed, or
    - are infertile for any other medical reason and this infertility is permanent and cannot be reversed.
- Females who can become pregnant should use effective birth control before starting treatment with VANRAFIA, during treatment with VANRAFIA and for 2 weeks after stopping VANRAFIA because the medicine may still be in your body.
  - Talk with your healthcare provider or gynecologist (a healthcare provider who specializes in reproduction) to find out about options for effective forms of birth control that you may use to prevent pregnancy during treatment with VANRAFIA.
  - If you decide that you want to change the form of birth control that you use, talk with your healthcare provider or gynecologist to be sure that you choose another effective form of birth control.
- Do not have unprotected sex. Talk to your healthcare provider or pharmacist right away if you have unprotected sex or if you think your birth control has failed. Your healthcare provider may talk with you about using emergency birth control.
- Tell your healthcare provider right away if you miss a menstrual period or think you may be pregnant.

See “What are the possible side effects of VANRAFIA?” for more information about side effects.

What is VANRAFIA?
VANRAFIA is a prescription medicine used to reduce levels of protein in the urine (proteinuria) in adults with a kidney disease called primary immunoglobulin A nephropathy (IgAN) who are at risk of their disease getting worse quickly.
It is not known if VANRAFIA is safe and effective in children.

Who should not take VANRAFIA?
Do not take VANRAFIA if you are

- pregnant, plan to become pregnant, or become pregnant during treatment with VANRAFIA. VANRAFIA can cause serious birth defects. See “What is the most important information I should know about VANRAFIA?”
- allergic to atrasentan or any of the ingredients in VANRAFIA. See the end of this Medication Guide for a complete list of ingredients in VANRAFIA.

Before taking VANRAFIA, tell your healthcare provider about all your medical conditions including if you:

- have liver problems
- are pregnant or plan to become pregnant during VANRAFIA treatment. VANRAFIA can cause serious birth defects. See "What is the most important information I should know about VANRAFIA?”
- are breastfeeding or plan to breastfeed. It is not known if VANRAFIA passes into your breast milk. Do not breastfeed during treatment with VANRAFIA. Talk with your healthcare provider about the best way to feed your baby if you take VANRAFIA.

Tell your healthcare provider about all the medicines you take, including prescription and over-the-counter medicines, vitamins, and herbal supplements. Taking VANRAFIA with certain other medicines may affect the way VANRAFIA, and the other medicine works and may increase your risk for side effects. Do not start any new medicine until you check with your healthcare provider.

How should I take VANRAFIA?

- Take VANRAFIA exactly as your healthcare provider tells you. Do not change your dose or stop taking unless your healthcare provider tells you to.
- Take 1 VANRAFIA tablet 1 time each day with or without food.
- Swallow VANRAFIA tablets whole. Do not cut, crush, or chew VANRAFIA tablets.
- If you miss a dose or more doses of VANRAFIA, skip the missed dose and take your next dose at your regularly scheduled time. Do not take 2 doses at the same time to make up for a missed dose.
- If you take too much VANRAFIA, call your healthcare provider right away or go to the nearest hospital or emergency room.

What are the possible side effects of VANRAFIA?
VANRAFIA can cause serious side effects, including:

- Serious birth defects. See "What is the most important information I should know about VANRAFIA?”
- Liver problems. Medicines like VANRAFIA can cause liver problems, including liver failure. VANRAFIA can increase liver enzymes in your blood. Your healthcare provider will do blood tests to check your liver enzymes before starting treatment and if needed during treatment. Your healthcare provider may temporarily stop or permanently stop treatment with VANRAFIA if your liver enzymes increase or if you develop symptoms of liver problems. Tell your healthcare provider if you develop any of the following symptoms of liver problems during treatment with VANRAFIA.

- nausea or vomiting
- pain in the upper right stomach
- tiredness
- loss of appetite

- yellowing of your skin or whites of your eyes
- dark urine
- fever
- itching

- Fluid retention. VANRAFIA can cause your body to hold too much water. Tell your healthcare provider if you develop any unusual weight gain, trouble breathing, or swelling of your ankles or legs during treatment. Your healthcare provider may prescribe other medicines (diuretics) and may temporarily stop VANRAFIA if you develop fluid retention.
- Decreased sperm count. VANRAFIA may cause decreased sperm counts in males and may affect the ability to father a child. Tell your healthcare provider if being able to have children is important to you.

The most common side effects of VANRAFIA include:

- swelling of hands, legs, ankles, and feet (peripheral edema)
- low red blood cells (anemia)

These are not all of the possible side effects of VANRAFIA. Call your healthcare provider for medical advice about side effects. You may report side effects to FDA at 1-800-FDA-1088.

How should I store VANRAFIA?

- Store VANRAFIA at room temperature between 68°F to 77°F (20°C to 25°C).
- Store VANRAFIA in the original container.
- The bottle has a child-resistant cap and contains a desiccant to help keep the tablets dry.

Keep VANRAFIA and all medicines out of the reach of children.

General information about the safe and effective use of VANRAFIA
Medicines are sometimes prescribed for purposes other than those listed in the Medication Guide. Do not use VANRAFIA for a condition for which it was not prescribed. Do not give VANRAFIA to other people, even if they have the same symptoms that you have. It may harm them. You can ask your pharmacist or healthcare provider for information about VANRAFIA that is written for health professionals.

What are the ingredients in VANRAFIA?
Active ingredient: atrasentan
Inactive ingredients: crospovidone, glyceryl dibehenate, hypromellose, lactose monohydrate, L-cysteine hydrochloride monohydrate, polyethylene glycol, and silicon dioxide.

Distributed by: Novartis Pharmaceuticals Corporation, East Hanover, New Jersey 07936
© 2025 Novartis
For more information, go to www.VANRAFIA.com or call 1-888-669-6682.

This Medication Guide has been approved by the U.S. Food and Drug Administration.

Issued: April 2025

T2025-19

PRINCIPAL DISPLAY PANEL

NDC 0078-1420-15

Rx only

VANRAFIA™

(atrasentan) tablets

0.75 mg

Dispense with accompanying
Medication Guide.

Swallow tablets whole.
Do not cut, crush, or chew.

30 tablets

NOVARTIS